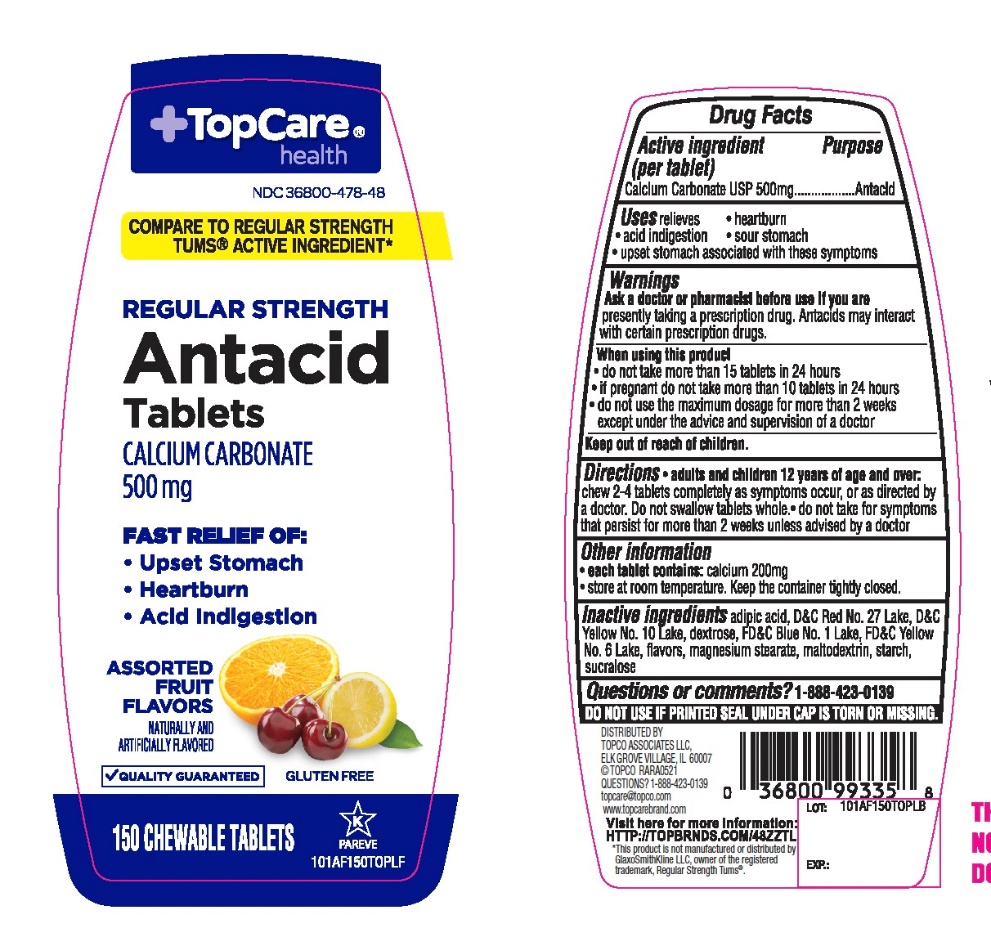 DRUG LABEL: Topcare Antacid Calcium
NDC: 36800-478 | Form: TABLET, CHEWABLE
Manufacturer: Topco Associates LLC.
Category: otc | Type: HUMAN OTC DRUG LABEL
Date: 20251108

ACTIVE INGREDIENTS: CALCIUM CARBONATE 500 mg/1 1
INACTIVE INGREDIENTS: ADIPIC ACID; D&C RED NO. 27; D&C YELLOW NO. 10; DEXTROSE, UNSPECIFIED FORM; FD&C BLUE NO. 1; FD&C YELLOW NO. 6; MAGNESIUM STEARATE; MALTODEXTRIN; STARCH, CORN; SUCRALOSE

Topco Associates LLC. Antacid Calcium Drug Facts

Active ingredient (per tablet)

Calcium Carbonate USP 500mg

Purpose

Antacid

Uses

relieves

- heartburn
- acid indigestion
- sour stomach
- upset stomach associated with these symptoms

Warnings

Ask a doctor or pharmacist before use if you arepresently taking a prescription drug. Antacids may interact with certain prescription drugs.

When using this product

- do not take more than 15 tablets in 24 hours
- if pregnant do not take more than 10 tablets in 24 hours
- do not use the maximum dosage for more than 2 weeks except under the advice and supervision of a doctor.

Directions

- adults and children 12 years of age and over:chew 2-4 tablets as symptoms occur, or as directed by a doctor
- do not take for symptoms that persist for more than 2 weeks unless advised by a doctor

Other information

- each tablet contains: elemental calcium 200mg
- Store at room temperature. Keep the container tightly closed.

Inactive ingredients

adipic acid, D & C red # 27 lake, D&C yellow # 10 lake, dextrose, FD&C blue #1 lake, FD&C yellow #6 lake, flavors, magnesium stearate, maltodextrin, starch, sucralose.

Questions?

1-888-423-0139

Safety sealed: Do not use if printed seal under cap is torn or missing

Package/Label Principal Display Panel

NDC # 36800-478-48

+ TopCare®healthTM

COMPARE TO REGULAR STRENGTH TUMS® ACTIVE INGREDIENT*

Regular Strength

Antacid Tablets

Calcium Carbonate 500 mg

FAST RELIEF OF:

- Upset Stomach
- Heartburn
- Acid indigestion

ASSORTED FRUIT FLAVORS

150 CHEWABLE TABLETS

GLUTEN- FREE

QUALITY GUARANTEED

For questions or comments, please call

1-888-423-0139.

Distributed by: TOPCO ASSOCIATES LLC

1. ELK GROVE VILLAGE, IL 6007
2. © TOPCO RARA0918

QUESTIONS? 1-888-423-0139

topcare@topco.comwww.topcarebrand.com

Visit here for more information: http://topbrnds.com/48ZS0K

*This product is not manufactured or distributed by GlaxoSmithKline LLC, owner of the registered trademark, Regular Strength Tums®.